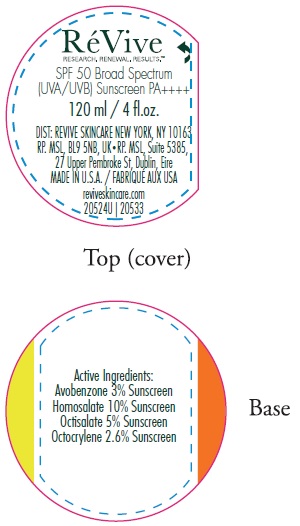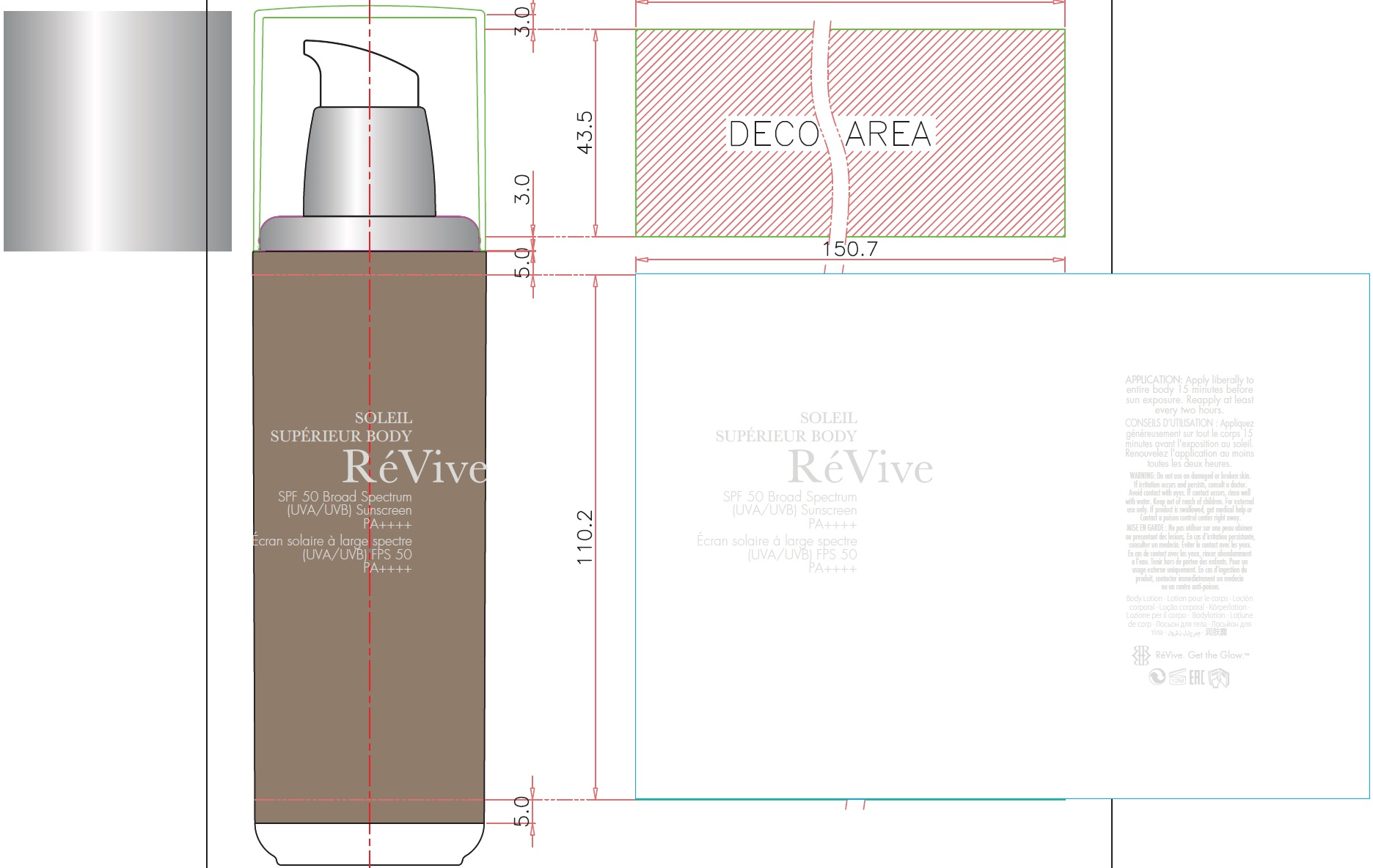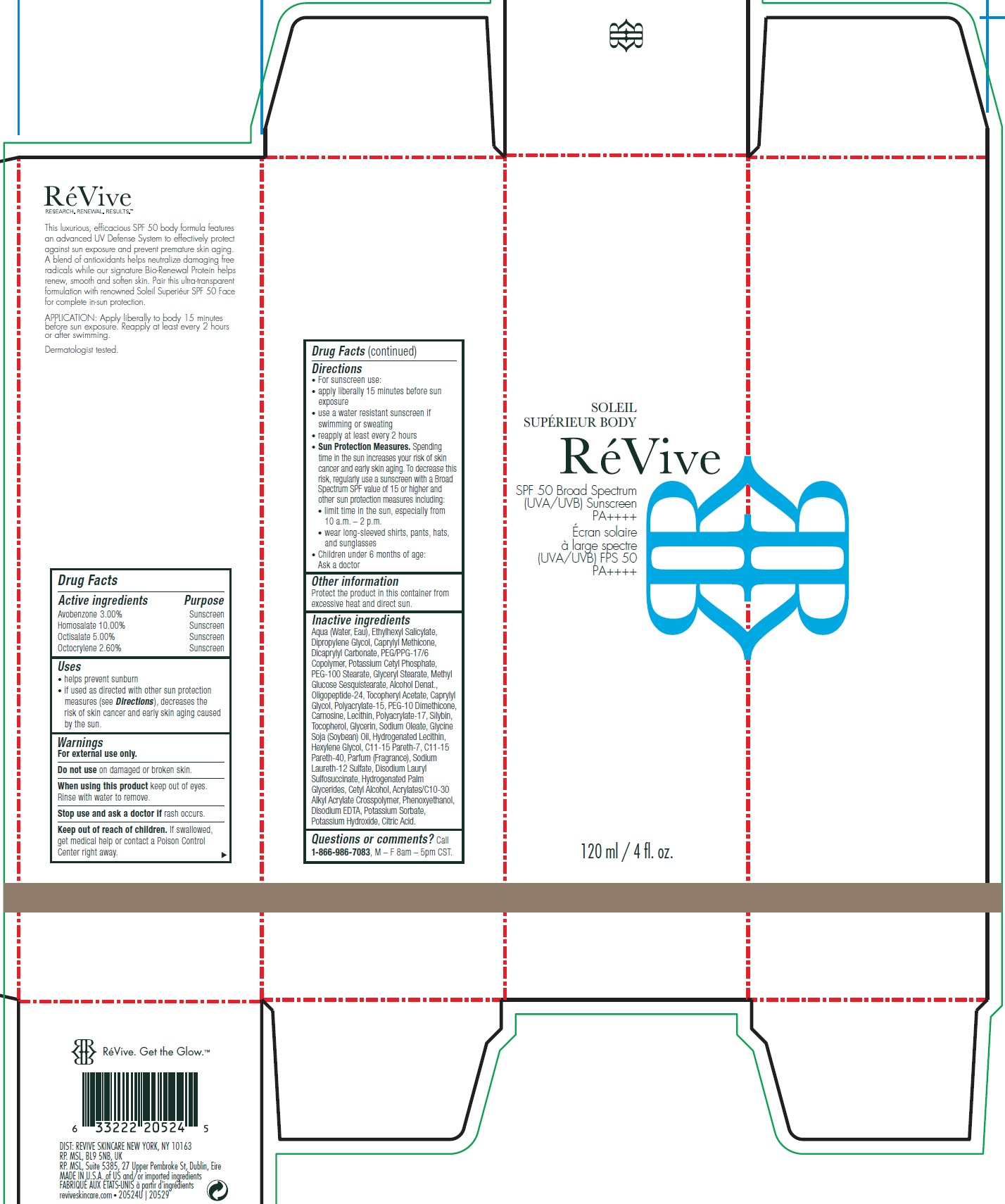 DRUG LABEL: Soleil Superieur Body SPF 50 US
NDC: 82691-145 | Form: CREAM
Manufacturer: RV Skincare LLC
Category: otc | Type: HUMAN OTC DRUG LABEL
Date: 20231106

ACTIVE INGREDIENTS: AVOBENZONE 30 mg/1 mL; HOMOSALATE 100 mg/1 mL; OCTISALATE 50 mg/1 mL; OCTOCRYLENE 26 mg/1 mL
INACTIVE INGREDIENTS: WATER; DIPROPYLENE GLYCOL; CAPRYLYL TRISILOXANE; DICAPRYLYL CARBONATE; PEG/PPG-17/6 COPOLYMER; POTASSIUM CETYL PHOSPHATE; PEG-100 STEARATE; GLYCERYL MONOSTEARATE; METHYL GLUCOSE SESQUISTEARATE; ALCOHOL; .ALPHA.-TOCOPHEROL ACETATE; CAPRYLYL GLYCOL; CARNOSINE; SILIBININ; TOCOPHEROL; GLYCERIN; SODIUM OLEATE; SOYBEAN OIL; HEXYLENE GLYCOL; C11-15 PARETH-7; C11-15 PARETH-40; SODIUM LAURETH-12 SULFATE; DISODIUM LAURYL SULFOSUCCINATE; HYDROGENATED PALM GLYCERIDES; CETYL ALCOHOL; PHENOXYETHANOL; EDETATE DISODIUM ANHYDROUS; POTASSIUM SORBATE; POTASSIUM HYDROXIDE; CITRIC ACID MONOHYDRATE

Soleil Superieur Body SPF 50 US

Active ingredients

Avobenzone 3.00%

Homosalate 10.00%

Octisalate 5.00%

Octocrylene 2.60%

Purpose

Sunscreen

Uses

• helps prevent sunburn

• if used as directed with other sun protection measures (see), decreases the risk of skin cancer and early skin aging caused by the sun. Directions

Warnings

For external use only.

Do not use

on damaged or broken skin.

When using this product

keep out of eyes. Rinse with water to remove.

Stop use and ask a doctor if

rash occurs.

Keep out of reach of children.

If swallowed, get medical help or contact a Poison Control Center right away.

Directions

• For sunscreen use: • apply liberally 15 minutes before sun exposure • use a water resistant sunscreen if swimming or sweating • reapply at least every 2 hours • Spending time in the sun increases your risk of skin cancer and early skin aging. To decrease this risk, regularly use a sunscreen with a Broad Spectrum SPF value of 15 or higher and other sun protection measures including: • limit time in the sun, especially from 10 a.m. – 2 p.m. • wear long-sleeved shirts, pants, hats, and sunglasses • Children under 6 months of age: Ask a doctor
Sun Protection Measures.

Other information

Protect the product in this container from excessive heat and direct sun.

Inactive ingredients:

Aqua (Water, Eau), Ethylhexyl Salicylate, Dipropylene Glycol, Caprylyl Methicone, Dicaprylyl Carbonate, PEG/PPG-17/6 Copolymer, Potassium Cetyl Phosphate, PEG-100 Stearate, Glyceryl Stearate, Methyl Glucose Sesquistearate, Alcohol Denat., Oligopeptide-24, Tocopheryl Acetate, Caprylyl Glycol, Polyacrylate-15, PEG-10 Dimethicone, Carnosine, Lecithin, Polyacrylate-17, Silybin, Tocopherol, Glycerin, Sodium Oleate, Glycine Soja (Soybean) Oil, Hydrogenated Lecithin, Hexylene Glycol, C11-15 Pareth-7, C11-15 Pareth-40, Parfum (Fragrance), Sodium Laureth-12 Sulfate, Disodium Lauryl Sulfosuccinate, Hydrogenated Palm Glycerides, Cetyl Alcohol, Acrylates/C10-30 Alkyl Acrylate Crosspolymer, Phenoxyethanol, Disodium EDTA, Potassium Sorbate, Potassium Hydroxide, Citric Acid.

Questions or comments?

Call , M – F 8am – 5pm CST. 1-866-986-7083